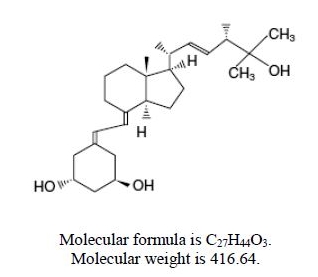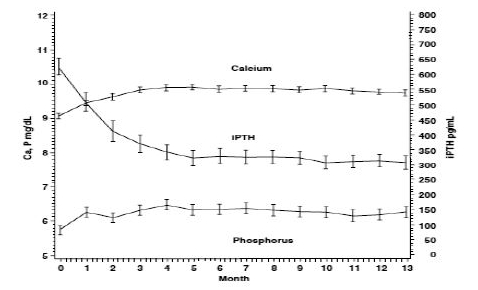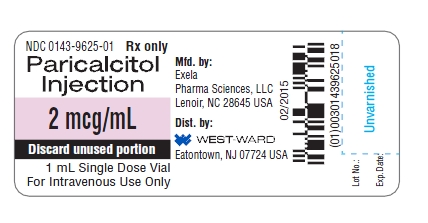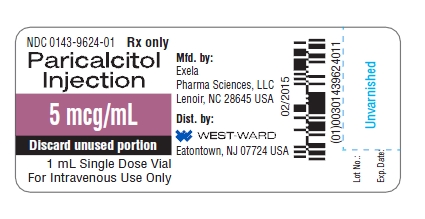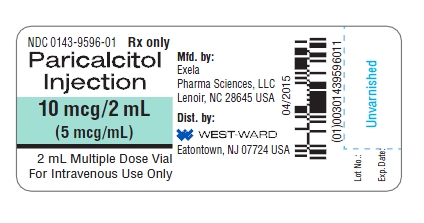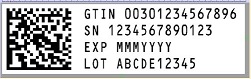 DRUG LABEL: Paricalcitol
NDC: 0143-9625 | Form: INJECTION
Manufacturer: West-Ward Pharmaceuticals Corp
Category: prescription | Type: HUMAN PRESCRIPTION DRUG LABEL
Date: 20181212

ACTIVE INGREDIENTS: PARICALCITOL 2 ug/1 mL
INACTIVE INGREDIENTS: ALCOHOL; SORBITOL; WATER

HIGHLIGHTS OF PRESCRIBING INFORMATION

These highlights do not include all the information needed to use PARICALCITOL INJECTION safely and effectively. See full prescribing information for PARICALCITOL INJECTION.
PARICALCITOL INJECTION, for intravenous use
Initial U.S. Approval: 1998

1 INDICATIONS AND USAGE

Paricalcitol Injection is an active vitamin D2 analog indicated for the prevention and treatment of secondary hyperparathyroidism associated with chronic kidney disease Stage 5. (1)

2 DOSAGE AND ADMINISTRATION

- The recommended starting dose is 0.04 mcg/kg to 0.1 mcg/kg (2.8 – 7 mcg).
- Administer Paricalcitol Injection as a bolus through a hemodialysis vascular access port at any time during dialysis. Dosing should not occur more frequently than every other day.
- Do not inject Paricalcitol Injection directly into a vein.
- Paricalcitol Injection dose should be individualized. If a satisfactory PTH lowering response is not observed with the initial dose, the dose may be increased by 2 to 4 mcg at 2- to 4- week intervals based on parathyroid hormone (PTH) levels. (2)

Suggested Dosage Adjustment

PTH Level at Follow-up Visit | Dosage Adjustment
Above target and PTH increased | Increase
Above target and PTH decreased by less than 30% | Increase
Above target and PTH decreased by 30 to 60% | No Change
Above target and PTH decreased by more than 60% | Decrease
At target and PTH stable | No Change

3 DOSAGE FORMS AND STRENGTHS

Paricalcitol Injection is available in the following presentations: 2 mcg per mL single dose vial, 5 mcg per mL single dose vial, 10 mcg per 2 mL (5 mcg per mL) multiple dose vial. (3)

4 CONTRAINDICATIONS

Evidence of hypercalcemia, vitamin D toxicity or hypersensitivity. (4)

5 WARNINGS AND PRECAUTIONS

- Hypercalcemia: The risk may be increased when Paricalcitol Injection is used concomitantly with high dose calcium preparations, thiazide diuretics, or metabolically inactive or active forms of vitamin D. Monitor serum calcium when using Paricalcitol Injection and adjust dose accordingly. (5.1)
- Digitalis Toxicity: Hypercalcemia increases the risk of digitalis toxicity. In patients using Paricalcitol Injection concomitantly with digitalis compounds, monitor both serum calcium and patients for signs and symptoms of digitalis toxicity and increase frequency of monitoring when initiating or adjusting the dose of Paricalcitol Injection. (5.2)
- Risk of Increased Paricalcitol Levels With Concomitant Use of Strong CYP3A Inhibitors: Use of Paricalcitol Injection with strong CYP3A inhibitors increases the concentration of paricalcitol in the blood. In patients on Paricalcitol Injection who are initiating or discontinuing drugs known to be strong CYP3A inhibitors, monitor serum calcium and PTH more frequently and adjust Paricalcitol Injection dose as required. (5.3)
- Adynamic Bone Disease: May develop if PTH levels are suppressed to abnormally low levels. Monitor PTH levels and adjust Paricalcitol Injection accordingly. (5.4)

6 ADVERSE REACTIONS

The most common adverse reactions (greater than 5% and more frequent than placebo) include nausea, vomiting and edema. (6.1)

To report SUSPECTED ADVERSE REACTIONS, contact West-Ward Pharmaceutical Corp. at 1-877-233-2001 or FDA at 1-800-FDA-1088 or www.fda.gov/medwatch.

7 DRUG INTERACTIONS

Co-administration with strong CYP3A inhibitors (e.g. ketoconazole) increases paricalcitol blood levels. See WARNINGS AND PRECAUTIONS. (5.3, 7.1)

8 USE IN SPECIFIC POPULATIONS

- Pregnancy: Use during pregnancy only if the potential benefit justifies the potential risk. (8.1)
- Nursing Mothers: A decision should be made whether to discontinue nursing or to discontinue the drug, taking into account the importance of the drug to the mother. (8.3)

FULL PRESCRIBING INFORMATION

1 INDICATIONS AND USAGE

Paricalcitol Injection is an active vitamin D2 analogue indicated for the prevention and treatment of secondary hyperparathyroidism associated with chronic kidney disease (CKD) Stage 5.

2 DOSAGE AND ADMINISTRATION

For intravenous use through hemodialysis vascular access port only.

The recommended starting dose of Paricalcitol Injection is 0.04 mcg/kg to 0.1 mcg/kg (2.8 – 7 mcg) administered through a hemodialysis vascular access port as a bolus dose at any time during dialysis. Dosing should not occur more frequently than every other day. The drug product should not be injected directly into a vein. Dosage should be individualized. If a satisfactory parathyroid hormone (PTH) lowering response is not observed using the recommended starting dose, the dose may be increased by 2 to 4 mcg every 2 to 4 weeks based on PTH levels (refer to Table 1).

Table 1: Suggested Dosage Adjustment
PTH Level at Follow-up Visit | Dosage Adjustment
Above target and PTH increased | Increase
Above target and PTH decreased by less than 30% | Increase
Above target and PTH decreased by 30 to 60% | No Change
Above target and PTH decreased by more than 60% | Decrease
At target and PTH stable | No Change

When initiating Paricalcitol Injection or adjusting Paricalcitol Injection dose, measure serum calcium and phosphorus frequently (e.g., twice weekly) and PTH every 2 to 4 weeks. Once a maintenance dose has been established, serum calcium and phosphorus should be measured at least monthly and plasma PTH every 3 months.

3 DOSAGE FORMS AND STRENGTHS

Paricalcitol Injection is available in the following presentations:

- 2 mcg per mL single dose vial
- 5 mcg per mL single dose vial
- 10 mcg per 2 mL (5 mcg per mL) multiple dose vial

4 CONTRAINDICATIONS

Paricalcitol Injection is contraindicated in patients with evidence of:

- Hypercalcemia [see Warnings and Precautions (5.1)]
- Vitamin D toxicity [see Warnings and Precautions (5.1)] or
- Hypersensitivity to paricalcitol or any inactive ingredient in this product [see Adverse Reactions (6.2)]

5 WARNINGS AND PRECAUTIONS

5.1 Hypercalcemia

Hypercalcemia may occur during Paricalcitol Injection treatment and may be exacerbated by concomitant administration of high doses of calcium containing preparations, thiazide diuretics, or vitamin D (i.e., all forms). Acute hypercalcemia may exacerbate tendencies for cardiac arrhythmias and seizures and may potentiate the effect of digitalis on the heart. Chronic hypercalcemia can lead to generalized vascular calcification and other soft-tissue calcification. Hypercalcemia may be so severe as to require emergency attention.

High intake of calcium and phosphate concomitantly with vitamin D compounds may lead to hypercalcemia, hypercalciuria, and hyperphosphatemia. Prevention of such adverse reactions requires frequent serum calcium monitoring and careful Paricalcitol Injection dose adjustments.

Concomitant use with other active vitamin D analogues should be avoided during Paricalcitol Injection treatment to prevent hypercalcemia.

Patients also should be informed about the symptoms of elevated calcium, which include feeling tired, difficulty thinking clearly, loss of appetite, nausea, vomiting, constipation, increased thirst, increased urination and weight loss.

5.2 Digitalis Toxicity

Hypercalcemia of any cause increases the risk of digitalis toxicity. In patients using Paricalcitol Injection concomitantly with digitalis compounds, monitor both serum calcium and patients for signs and symptoms of digitalis toxicity and increase frequency of monitoring when initiating or adjusting the dose of Paricalcitol Injection [see Dosage and Administration (2)].

5.3 Risk of Increased Paricalcitol Levels With Concomitant Use of Strong CYP3A Inhibitors

Concomitant use of Paricalcitol Injection with strong CYP3A inhibitors will increase the levels of paricalcitol in the blood. In patients on Paricalcitol Injection who are initiating or discontinuing therapy with drugs known to be strong CYP3A inhibitors, monitor serum calcium and PTH more frequently and adjust Paricalcitol Injection dose as required [see Drug Interactions (7.1), Clinical Pharmacology (12.3)].

5.4 Adynamic Bone Disease

Adynamic bone disease with subsequent increased risk of fractures may develop if PTH levels are suppressed to abnormally low levels. Monitor PTH levels and adjust Paricalcitol Injection dose [see Dosage and Administration (2)].

6 ADVERSE REACTIONS

6.1 Clinical Trials Experience

Because clinical studies are conducted under widely varying conditions, adverse reaction rates observed in the clinical studies of a drug cannot be directly compared to rates in the clinical studies of another drug and may not reflect the rates observed in practice.

Safety has been evaluated in clinical studies conducted with another paricalcitol injection product in 609 patients with CKD Stage 5. In four, placebo-controlled, double-blind, multicenter studies, discontinuation of therapy due to any adverse event occurred in 6.5% of 62 patients treated with paricalcitol injection (dosage titrated as tolerated, [see Clinical Studies (14)]) and 2% of 51 patients treated with placebo for 1 to 3 months. Adverse reactions occurring with greater frequency in the paricalcitol group and at a frequency of 2% or greater are presented in the following table:

Table 2: Adverse Reactions Occurring at a Rate [A patient who reported the same medical term more than once was counted only once for that medical term.] of 2% or Greater in CKD Stage 5 Patients in Four Placebo-Controlled Studies
Adverse Reaction | Placebo (n=51) % | Paricalcitol Injection (n=62) %
Cardiac Disorders
Palpitations | 0.0 | 3.2
Gastrointestinal Disorders
Nausea | 7.8 | 12.9
Vomiting | 5.9 | 8.1
Gastrointestinal Hemorrhage | 2.0 | 4.8
Dry Mouth | 2.0 | 3.2
General Disorders and Administration Site Conditions
Edema | 0.0 | 6.5
Chills | 2.0 | 4.8
Pyrexia | 2.0 | 4.8
Malaise | 0.0 | 3.2
Infections and Infestations
Pneumonia | 0.0 | 4.8
Sepsis | 2.0 | 4.8
Influenza | 3.9 | 4.8
Musculoskeletal and Connective Tissue Disorders
Arthralgia | 3.9 | 4.8

Specific laboratory parameters [i.e., changes in mean Calcium (Ca), Phosphorus (P), and Calcium Phosphorus product (Ca × P)] were followed in an open-label safety study conducted with another paricalcitol injection product for up to 13 months in duration in this patient population and results are shown below [see Clinical Studies (14)].

Other Adverse Reactions Associated with Paricalcitol Injection Use

The following adverse reactions occurred in less than 2% of the paricalcitol-treated patients in the above mentioned double-blind, placebo-controlled clinical trials and in additional double-blind, active-controlled and open-label studies:

Blood and Lymphatic System Disorders: Anemia, lymphadenopathy

Cardiac Disorders: Arrhythmia, atrial flutter, cardiac arrest

Ear and Labyrinth Disorders: Ear discomfort

Endocrine Disorders: Hypoparathyroidism

Eye Disorders: Conjunctivitis, glaucoma, ocular hyperemia

Gastrointestinal Disorders: Abdominal discomfort, constipation, diarrhea, dysphagia, gastritis, intestinal ischemia, rectal hemorrhage

General Disorders and Administration Site Conditions: Asthenia, chest discomfort, chest pain, condition aggravated, edema peripheral, fatigue, feeling abnormal, gait disturbance, injection site extravasation, injection site pain, pain, swelling, thirst

Infections and Infestations: Nasopharyngitis, upper respiratory tract infection, vaginal infection

Laboratory Investigations and Vital Signs: Increased aspartate aminotransferase, prolonged bleeding time, irregular heart rate, decreased weight

Metabolism and Nutrition Disorders: Decreased appetite, hypercalcemia, hyperkalemia, hyperphosphatemia, hypocalcemia

Musculoskeletal and Connective Tissue Disorders: Joint stiffness, muscle twitching, myalgia

Neoplasms Benign, Malignant and Unspecified: Breast cancer

Nervous System Disorders: Cerebrovascular accident, dizziness, dysgeusia, headache, hypoesthesia, myoclonus, paresthesia, syncope, unresponsive to stimuli

Psychiatric Disorders: Agitation, confusional state, delirium, insomnia, nervousness, restlessness

Reproductive System and Breast Disorders: Breast pain, erectile dysfunction

Respiratory, Thoracic and Mediastinal Disorders: Cough, dyspnea, orthopnea, pulmonary edema, wheezing

Skin and Subcutaneous Tissue Disorders: Alopecia, blister, hirsutism, night sweats, rash pruritic, pruritus, skin burning sensation

Vascular Disorders: Hypertension, hypotension

6.2 Postmarketing Experience

The following adverse reactions have been identified during post approval use of another paricalcitol injection product. Because these reactions are reported voluntarily from a population of uncertain size, it is not always possible to reliably estimate their frequency or establish a causal relationship to drug exposure.

Allergic reactions including rash, urticaria, and angioedema (including laryngeal edema) have been reported.

7 DRUG INTERACTIONS

7.1 Strong CYP3A Inhibitors

Paricalcitol is partially metabolized by CYP3A. Paricalcitol blood levels will be increased when paricalcitol is co-administered with strong CYP3A inhibitors. If a patient initiates or discontinues therapy with a strong CYP3A inhibitor, monitor both PTH and serum calcium more frequently and adjust Paricalcitol Injection dose as required [see Clinical Pharmacology (12.3)].

8 USE IN SPECIFIC POPULATIONS

8.1 Pregnancy

Pregnancy Category C

Paricalcitol has been shown to cause minimal decreases in fetal viability (5%) when administered daily to rabbits at a dose 0.5 times the 0.24 mcg/kg human dose (based on surface area, mg/m^2) and when administered to rats at a dose 2 times the 0.24 mcg/kg human dose (based on plasma levels of exposure). At the highest dose tested (20 mcg/kg 3 times per week in rats, 13 times the 0.24 mcg/kg human dose based on surface area), there was a significant increase of the mortality of newborn rats at doses that were maternally toxic (hypercalcemia). No other effects on offspring development were observed. Paricalcitol was not teratogenic at the doses tested.

There are no adequate and well-controlled studies in pregnant women. Paricalcitol Injection should be used during pregnancy only if the potential benefit to the mother justifies the potential risk to the fetus.

8.3 Nursing Mothers

Studies in rats have shown that paricalcitol is present in the milk. It is not known whether paricalcitol is excreted in human milk. In the nursing patient, a decision should be made whether to discontinue nursing or to discontinue the drug, taking into account the importance of the drug to the mother.

8.4 Pediatric Use

The safety and effectiveness of paricalcitol injection were examined with another paricalcitol injection product in a 12-week randomized, double-blind, placebo-controlled study of 29 pediatric patients, aged 5-19 years, with end-stage renal disease on hemodialysis and nearly all had received some form of vitamin D prior to the study. Seventy-six percent of the patients were male, 52% were Caucasian and 45% were African-American. The initial dose of paricalcitol injection was 0.04 mcg/kg 3 times per week based on baseline iPTH level of less than 500 pg/mL, or 0.08 mcg/kg 3 times a week, based on baseline iPTH level of ≥ 500 pg/mL, respectively. The dose of paricalcitol injection was adjusted in 0.04 mcg/kg increments based on the levels of serum iPTH, calcium and Ca x P. The mean baseline levels of iPTH were 841 pg/mL for the 15 paricalcitol injection-treated patients and 740 pg/mL for the 14 placebo-treated subjects. The mean dose of paricalcitol injection administered was 4.6 mcg (range: 0.8 mcg-9.6 mcg). Ten of the 15 (67%) paricalcitol injection-treated patients and 2 of the 14 (14%) placebo-treated patients completed the trial. Ten of the placebo patients (71%) were discontinued due to excessive elevations in iPTH levels as defined by 2 consecutive iPTH levels > 700 pg/mL and greater than baseline after 4 weeks of treatment.

In the primary efficacy analysis, 9 of 15 (60%) subjects in the paricalcitol injection group had 2 consecutive 30% decreases from baseline iPTH compared with 3 of 14 (21%) patients in the placebo group (95% CI for the difference between groups -1%, 63%). Twenty-three percent of paricalcitol injection vs. 31% of placebo patients had at least one serum calcium level > 10.3 mg/dL and 40% vs. 14% of paricalcitol injection vs. placebo subjects had at least one Ca x P ion product > 72 (mg/dL)^2. The overall percentage of serum calcium measurements >10.3 mg/dL was 7% in the paricalcitol injection group and 7% in the placebo group; the overall percentage of patients with Ca x P product >72 (mg/dL)^2 was 8% in the paricalcitol injection group and 7% in the placebo group. No subjects in either the paricalcitol injection group or placebo group developed hypercalcemia (defined as at least one calcium value > 11.2 mg/dL) during the study.

8.5 Geriatric Use

Clinical studies of paricalcitol injection did not include sufficient numbers of subjects aged 65 and over to determine whether they respond differently from younger subjects. Other reported clinical experience has not identified differences in responses between the elderly and younger patients. In general, dose selection for an elderly patient should be cautious, usually starting at the low end of the dosing range, reflecting the greater frequency of decreased hepatic, renal, or cardiac function, and of concomitant disease or other drug therapy.

10 OVERDOSAGE

Overdosage of Paricalcitol Injection may lead to hypercalcemia, hypercalciuria, hyperphosphatemia, and oversuppression of PTH resulting in adynamic bone disease. [see Warnings and Precautions (5.1, 5.4)].

10.1 Treatment of Overdosage and Hypercalcemia

The treatment of acute overdosage should consist of supportive measures, discontinuation of drug administration and supplemental calcium, institution of a low calcium diet. Serum calcium levels should be measured until normocalcemia ensues. When serum calcium levels have returned to within normal limits, Paricalcitol Injection may be reinitiated at a lower dose.

Paricalcitol is not significantly removed by dialysis.

11 DESCRIPTION

Paricalcitol, USP, the active ingredient in Paricalcitol Injection, is a synthetically manufactured active vitamin D2 analog. It is a white powder chemically designated as 19-nor-1α,3β,25-trihydroxy-9,10-secoergosta-5(Z),7(E),22(E)-triene and has the following structural formula:

Paricalcitol Injection is available as a sterile, clear, colorless, aqueous solution for intravenous injection. Each mL contains paricalcitol 2 mcg or 5 mcg and the following inactive ingredients: alcohol, 35% (v/v) and 70% sorbitol solution 7% (v/v) in water for injection.

12 CLINICAL PHARMACOLOGY

12.1 Mechanism of Action

Preclinical and in vitro studies have demonstrated that paricalcitol's biological actions are mediated through binding of the vitamin D receptor (VDR), which results in the selective activation of vitamin D responsive pathways. Vitamin D and paricalcitol have been shown to reduce parathyroid hormone levels by inhibiting PTH synthesis and secretion.

12.3 Pharmacokinetics

Within two hours after administering paricalcitol intravenous doses ranging from 0.04 to 0.24 mcg/kg, concentrations of paricalcitol decreased rapidly; thereafter, concentrations of paricalcitol declined log-linearly. No accumulation of paricalcitol was observed with three times a week dosing.

Distribution: Paricalcitol is extensively bound to plasma proteins (≥ 99.8%). In healthy subjects, the steady state volume of distribution is approximately 23.8 L. The mean apparent volume of distribution following a 0.24 mcg/kg dose of paricalcitol in CKD Stage 5 subjects requiring hemodialysis (HD) and peritoneal dialysis (PD) is between 31 and 35 L.

Metabolism: After intravenous administration of a 0.48 mcg/kg dose of ^3H-paricalcitol, parent drug was extensively metabolized, with only about 2% of the dose eliminated unchanged in the feces and no parent drug found in the urine. Several metabolites were detected in both the urine and feces. Most of the systemic exposure was from the parent drug. Two minor metabolites, relative to paricalcitol, were detected in human plasma. One metabolite was identified as 24(R)-hydroxy paricalcitol, while the other metabolite was unidentified. The 24(R)-hydroxy paricalcitol is less active than paricalcitol in an in vivo rat model of PTH suppression.

In vitro data suggest that paricalcitol is metabolized by multiple hepatic and non-hepatic enzymes, including mitochondrial CYP24, as well as CYP3A4 and UGT1A4. The identified metabolites include the product of 24(R)-hydroxylation (present at low levels in plasma), as well as 24,26- and 24,28-dihydroxylation and direct glucuronidation.

Elimination: Paricalcitol is excreted primarily by hepatobiliary excretion. Approximately 63% of a radioactive dose was recovered in the feces and 19% was recovered in the urine in healthy subjects. In healthy subjects, the mean elimination half-life of paricalcitol is about five to seven hours over the studied dose range of 0.04 to 0.16 mcg/kg. The pharmacokinetics of paricalcitol has been studied in CKD Stage 5 subjects requiring hemodialysis (HD) and peritoneal dialysis (PD). The mean elimination half-life of paricalcitol after administration of 0.24 mcg/kg paricalcitol intravenous bolus dose in CKD Stage 5 HD and PD patients is 13.9 and 15.4 hours, respectively (Table 3).

Table 3: Mean ± SD Paricalcitol Pharmacokinetic Parameters in CKD Stage 5 Subjects Following Single 0.24 mcg/kg Intravenous Bolus Dose
 | CKD Stage 5 HD n = 14 | CKD Stage 5 PD n = 8
Cmax (ng/mL) | 1.680 ± 0.511 | 1.832 ± 0.315
AUC0-∞ (ng•h/mL) | 14.51 ± 4.12 | 16.01 ± 5.98
β (1/h) | 0.050 ± 0.023 | 0.045 ± 0.026
t1/2(h) [harmonic mean ± pseudo standard deviation, HD: hemodialysis, PD: peritoneal dialysis. The degree of accumulation was consistent with the half-life and dosing frequency.] | 13.9 ± 7.3 | 15.4 ± 10.5
CL (L/h) | 1.49 ± 0.60 | 1.54 ± 0.95
Vdβ (L) | 30.8 ± 7.5 | 34.9 ± 9.5

Specific Populations

Geriatric: The pharmacokinetics of paricalcitol has not been investigated in geriatric patients greater than 65 years.

Pediatric: The pharmacokinetics of paricalcitol has not been investigated in patients less than 18 years of age.

Gender: The pharmacokinetics of paricalcitol was gender independent.

Hepatic Impairment: The disposition of intravenous paricalcitol (0.24 mcg/kg) was compared in patients with mild (n=5) and moderate (n=5) hepatic impairment (as indicated by the Child-Pugh method) and subjects with normal hepatic function (n=10). The pharmacokinetics of unbound paricalcitol was similar across the range of hepatic function evaluated in this study. No dosing adjustment is required in patients with mild and moderate hepatic impairment. The influence of severe hepatic impairment on the pharmacokinetics of paricalcitol has not been evaluated.

Renal Impairment: The pharmacokinetics of paricalcitol has been studied in CKD Stage 5 subjects requiring hemodialysis (HD) and peritoneal dialysis (PD). Hemodialysis procedure has essentially no effect on paricalcitol elimination. However, compared to healthy subjects, CKD Stage 5 subjects showed a decreased CL and increased half-life.

Drug Interactions

An in vitro study indicates that paricalcitol is not an inhibitor of CYP1A2, CYP2A6, CYP2B6, CYP2C8, CYP2C9, CYP2C19, CYP2D6, CYP2E1, or CYP3A at concentrations up to 50 nM (21 ng/mL) (approximately 20-fold greater than that obtained after highest tested dose). In fresh primary cultured hepatocytes, the induction observed at paricalcitol concentrations up to 50 nM was less than two-fold for CYP2B6, CYP2C9 or CYP3A, where the positive controls rendered a six- to nineteen-fold induction. Hence, paricalcitol is not expected to inhibit or induce the clearance of drugs metabolized by these enzymes.

Drug interactions with Paricalcitol Injection have not been studied. The following studies have been performed with oral paricalcitol capsules.

Omeprazole

The pharmacokinetic interaction between paricalcitol capsule (16 mcg) and omeprazole (40 mg; oral), a strong inhibitor of CYP2C19, was investigated in a single dose, crossover study in healthy subjects. The pharmacokinetics of paricalcitol was unaffected when omeprazole was administrated approximately 2 hours prior to the paricalcitol dose.

Strong CYP3A Inhibitors

Ketoconazole

Although no data are available for the drug interaction between Paricalcitol Injection and ketoconazole, a strong inhibitor of CYP3A, the effect of multiple doses of ketoconazole administered as 200 mg BID for 5 days on the pharmacokinetics of paricalcitol capsule has been studied in healthy subjects. The Cmax of paricalcitol was minimally affected, but AUC0-∞ approximately doubled in the presence of ketoconazole. The mean half-life of paricalcitol was 17.0 hours in the presence of ketoconazole as compared to 9.8 hours, when paricalcitol was administered alone [see Drug Interactions (7.1)].

13 NONCLINICAL TOXICOLOGY

13.1 Carcinogenesis, Mutagenesis, Impairment of Fertility

In a 104-week carcinogenicity study in CD-1 mice conducted with paricalcitol, an increased incidence of uterine leiomyoma and leiomyosarcoma was observed at subcutaneous doses of 1, 3, 10 mcg/kg (2 to 15 times the AUC at a human dose of 14 mcg, equivalent to 0.24 mcg/kg based on AUC). The incidence rate of uterine leiomyoma was significantly different than the control group at the highest dose of 10 mcg/kg.

In a 104-week carcinogenicity study in rats conducted with paricalcitol, there was an increased incidence of benign adrenal pheochromocytoma at subcutaneous doses of 0.15, 0.5, 1.5 mcg/kg (< 1 to 7 times the exposure following a human dose of 14 mcg, equivalent to 0.24 mcg/kg based on AUC). The increased incidence of pheochromocytomas in rats may be related to the alteration of calcium homeostasis by paricalcitol.

Paricalcitol did not exhibit genetic toxicity in vitro with or without metabolic activation in the microbial mutagenesis assay (Ames Assay), mouse lymphoma mutagenesis assay (L5178Y), or a human lymphocyte cell chromosomal aberration assay. There was also no evidence of genetic toxicity in an in vivo mouse micronucleus assay. Paricalcitol had no effect on fertility (male or female) in rats at intravenous doses up to 20 mcg/kg/dose [equivalent to 13 times the highest recommended human dose (0.24 mcg/kg) based on surface area, mg/m^2].

14 CLINICAL STUDIES

In three 12-week, placebo-controlled, phase 3 studies conducted with another paricalcitol injection product in patients with Stage 5 chronic kidney disease on dialysis, the dose of paricalcitol was started at 0.04 mcg/kg 3 times per week. The dose was increased by 0.04 mcg/kg every 2 weeks until intact parathyroid hormone (iPTH) levels were decreased at least 30% from baseline, or a fifth escalation brought the dose to 0.24 mcg/kg, or iPTH fell to less than 100 pg/mL, or the Ca x P product was greater than 75 within any 2 week period, or serum calcium became greater than 11.5 mg/dL at any time.

Patients treated with paricalcitol achieved a mean iPTH reduction of 30% within 6 weeks. In these studies, there was no significant difference in the incidence of hypercalcemia or hyperphosphatemia between paricalcitol and placebo-treated patients. The results from these studies are as follows:

Table 4: Mean Changes from Baseline to Final Evaluation in PTH, Alkaline Phosphatase, Phosphorus and Calcium x Phosphorus Product in CKD Stage 5 Patients in Three Placebo-Controlled, Phase 3 Studies
 | Group (No. of Pts.) | Baseline Mean (Range) | Mean (SE) Change From Baseline to Final Evaluation
PTH (pg/mL) | paricalcitol (n=40) | 783 (291–2076) | -379 (43.7)
PTH (pg/mL) | placebo (n=38) | 745 (320 – 1671) | -69.6 (44.8)
Alkaline Phosphatase (U/L) | paricalcitol (n=31) | 150 (40 – 600) | -41.5 (10.6)
Alkaline Phosphatase (U/L) | placebo (n=34) | 169 (56 – 911) | +2.6 (10.1)
Phosphorus (mg/dL) | paricalcitol (n=40) | 5.8 (3.7 – 10.2) | +0.47 (0.3)
Phosphorus (mg/dL) | placebo (n=38) | 6.0 (2.8 – 8.8) | -0.47 (0.3)
Calcium x Phosphorus Product | paricalcitol (n=40) | 54 (32 – 106) | +7.9 (2.2)
Calcium x Phosphorus Product | placebo (n=38) | 54 (26 – 77) | -3.9 (2.3)

A long-term, open-label safety study of 164 CKD Stage 5 patients conducted with another paricalcitol injection product (mean dose of 7.5 mcg three times per week), demonstrated that mean serum Ca, P, and Ca x P remained within clinically appropriate ranges with PTH reduction (mean decrease of 319 pg/mL at 13 months).

Figure 1: Mean Values for Serum iPTH, Calcium and Phosphorus Over Time in CKD Stage 5 Patients in a Phase 3 Study

16 HOW SUPPLIED/STORAGE AND HANDLING

Paricalcitol Injection is available in 2 mcg/mL single dose vials (NDC 0143-9625-25), 5 mcg/mL single dose vials (NDC 0143-9624-25) and 10 mcg/2 mL (5 mcg/mL) multiple dose vials (NDC 0143-9596-25) in cartons of 25 vials.

NDC Number |  | Volume/Container | Concentration | Total Content | Vial Type
0143-9625-25 |  | 1 mL/Fliptop Vial | 2 mcg/mL | 2 mcg | Single Dose
0143-9624-25 |  | 1 mL/Fliptop Vial | 5 mcg/mL | 5 mcg | Single Dose
0143-9596-25 |  | 2 mL/Fliptop Vial | 5 mcg/mL | 10 mcg | Multiple Dose

Store at 20° to 25°C (68° to 77°F) [see USP Controlled Room Temperature]. Do not freeze. After initial vial use, the contents of the multiple dose vial remain stable up to seven days when stored at controlled room temperature. Discard unused portion of the single dose vial.

Parenteral drug products should be inspected visually for particulate matter and discoloration prior to administration whenever solution and container permit.

17 PATIENT COUNSELING INFORMATION

Patients should be advised:

- of the most common adverse reactions with use of Paricalcitol Injection, which include nausea, vomiting and fluid retention.
- to adhere to instructions regarding diet and phosphorus restriction.
- to contact a health care provider if they develop symptoms of elevated calcium, (e.g. feeling tired, difficulty thinking clearly, loss of appetite, nausea, vomiting, constipation, increased thirst, increased urination and weight loss).
- to return to their dialysis clinic/health care provider’s office for routine monitoring. More frequent monitoring is necessary during the initiation of therapy, following dose changes or when potentially interacting medications are started or discontinued.
- to inform their health care provider of all medications, including prescription and nonprescription drugs, supplements, and herbal preparations they are taking and any change to their medical condition. Patients should also be advised to inform their health care provider prescribing a new medication that they are taking Paricalcitol Injection.

Manufactured by:
Exela Pharma Sciences, LLC
Lenoir, NC 28645 USA

Distributed by:
WEST-WARD PHARMACEUTICAL CORP.
Eatontown, NJ 07724 USA

9625-0415-00 April 2015

PRINCIPAL DISPLAY PANEL

NDC 0143-9625-01 Rx only
Paricalcitol
Injection
2 mcg/mL
Discard unused portion
1 mL Single Dose Vial
For Intravenous Use Only

PRINCIPAL DISPLAY PANEL

NDC 0143-9624-01 Rx only
Paricalcitol
Injection
5 mcg/mL
Discard unused portion
1 mL Single Dose Vial
For Intravenous Use Only

PRINCIPAL DISPLAY PANEL

NDC 0143-9596-01 Rx only
Paricalcitol
Injection
10 mcg/2 mL
(5 mcg/mL)
2 mL Multiple Dose Vial
For Intravenous Use Only